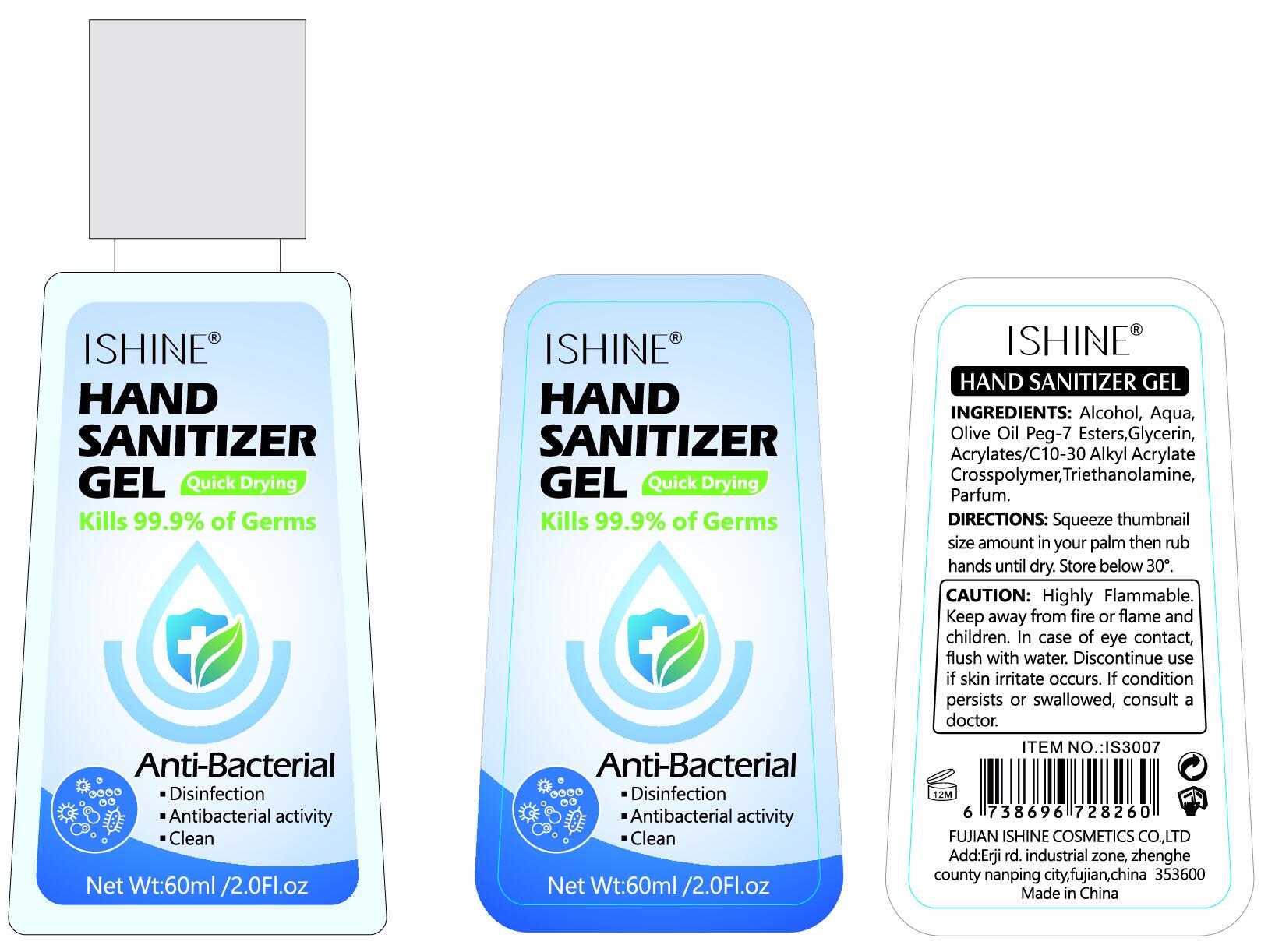 DRUG LABEL: ishine hand sanitizer
NDC: 54823-002 | Form: GEL
Manufacturer: Fujian Aishang Cosmetics Co., Ltd.
Category: otc | Type: HUMAN OTC DRUG LABEL
Date: 20200401

ACTIVE INGREDIENTS: ALCOHOL 45 mL/60 mL
INACTIVE INGREDIENTS: CARBOMER INTERPOLYMER TYPE A (55000 CPS); WATER; GLYCERIN; TROLAMINE; PEG-7 STEARATE

ACTIVE INGREDIENT

alcohol

INACTIVE INGREDIENT

water、OLIVE OIL PEG-7 ESTERS、GLYCERIN、ACRYLATES/C10-30 ALKYL ACRYLATE CROSSPOLYMER、TRIETHANOLAMINE、PARFUM

INDICATIONS AND USAGE

Squeeze thumbnail size amount in your palm then rub hands until dry.

DOSAGE AND ADMINISTRATION

Store below 30°.

WARNINGS

Highly Flammable.
Keep away from fire or flame and children. In case of eye contact, flush with water.

Discontinue use if skin irritate occurs. If condition persists or swallowed, consult a

keep out of reach of children